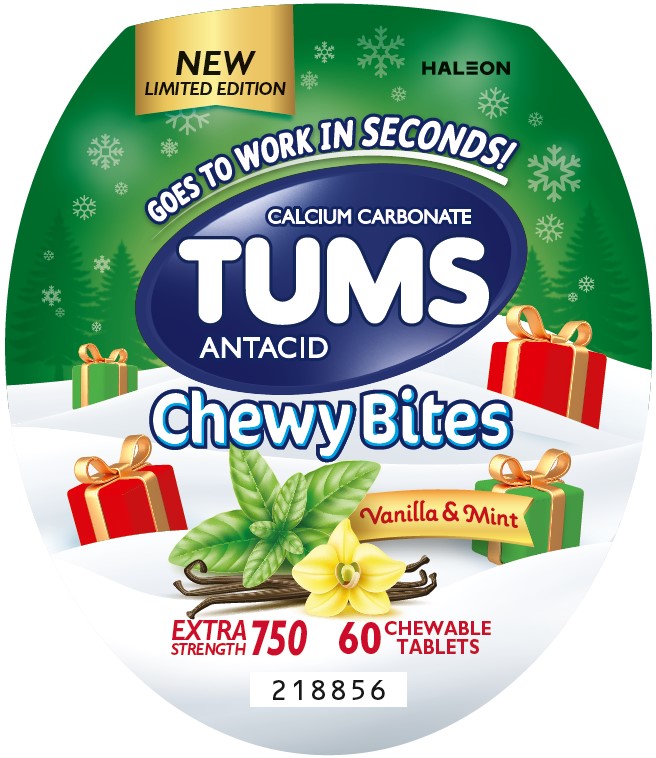 DRUG LABEL: Tums

NDC: 0135-5970 | Form: TABLET, CHEWABLE
Manufacturer: Haleon US Holdings LLC
Category: otc | Type: HUMAN OTC DRUG LABEL
Date: 20251119

ACTIVE INGREDIENTS: CALCIUM CARBONATE 750 mg/1 1
INACTIVE INGREDIENTS: ACACIA; YELLOW WAX; CARNAUBA WAX; CITRIC ACID MONOHYDRATE; COCONUT OIL; STARCH, CORN; CORN SYRUP; DEXTRIN, CORN; FD&C BLUE NO. 1 ALUMINUM LAKE; FD&C YELLOW NO. 5 ALUMINUM LAKE; MALTODEXTRIN; AMMONIUM GLYCYRRHIZATE; COPOVIDONE K25-31; PROPYLENE GLYCOL; WATER; SHELLAC; SODIUM BENZOATE; SORBIC ACID; SORBITOL; SOYBEAN LECITHIN; SUCRALOSE; TITANIUM DIOXIDE; CANOLA OIL

Drug Facts

Active ingredient (per tablet)

Calcium carbonate 750 mg

Purpose

Antacid

Uses

relieves

- heartburn
- acid indigestion
- sour stomach
- upset stomach associated with these symptoms

Warnings

Ask a doctor or pharmacist before use if you are

presently taking a prescription drug. Antacids may interact with certain prescription drugs.

When using this product

- do not take more than 6 tablets in 24 hours
- if pregnant do not take more than 6 tablets in 24 hours
- do not use the maximum dosage for more than 2 weeks, except under the advice and supervision of a doctor

Directions

- adults and children 12 years of age and over:chew 2-4 tablets as symptoms occur, or as directed by a doctor. Chew or crush tablets completely before swallowing.
- do not take for symptoms that persist for more than 2 weeks unless advised by a doctor

Other information

- each tablet contains:elemental calcium 300 mg
- do not store above 25°C (77°F)
- contains FD&C Yellow No. 5 (tartrazine) as a color additive

Inactive ingredients

acacia, beeswax, carnauba wax, citric acid, coconut oil, corn starch, corn syrup, dextrin, FD&C blue no. 1 aluminum lake, FD&C yellow no. 5 aluminum lake (tartrazine), maltodextrin, monoammoniated glycyrrhizin, natural and artificial flavors, pharmaceutical ink, polyvinylpyrrolidone, propylene glycol, purified water, shellac, sodium benzoate, sorbic acid, sorbitol, soy lecithin, sucrose, titanium dioxide, vegetable oil

Questions or comments?

1-800-452-0051

Additional Information

Do not use if printed inner safety seal under cap is broken or missing.

Principal Display Panel

NEWLIMITED EDITION

GOES TO WORK IN SECONDS!

CALCIUM CARBONATE

TUMS

ANTACID

Chewy Bites

Vanilla & Mint

EXTRA STRENGTH 750

60CHEWABLE TABLETS